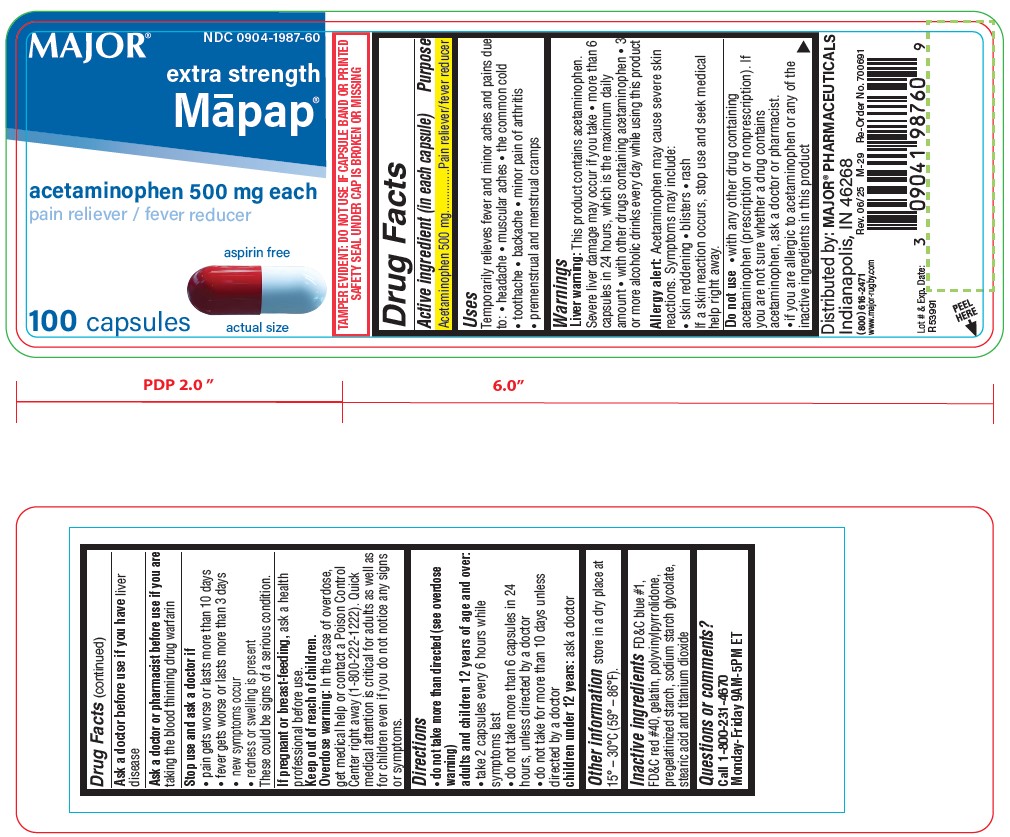 DRUG LABEL: MAPAP
NDC: 0904-1987 | Form: CAPSULE
Manufacturer: Major Pharmaceuticals
Category: otc | Type: HUMAN OTC DRUG LABEL
Date: 20251029

ACTIVE INGREDIENTS: ACETAMINOPHEN 500 mg/1 1
INACTIVE INGREDIENTS: FD&C BLUE NO. 1; FD&C RED NO. 40; GELATIN; POVIDONE K30; STARCH, CORN; SODIUM STARCH GLYCOLATE TYPE A POTATO; STEARIC ACID; TITANIUM DIOXIDE

0617 - Major

Drug Facts

Active ingredient (in each capsule)
Acetaminophen 500 mg

Purpose

Pain reliever/fever reducer

Uses

Temporarily relieves fever and minor aches and pains due to:

- headache
- muscular aches
- the common cold
- toothache
- backache
- minor pain of arthritis
- premenstrual and menstrual cramps

Warnings

Liver warning: This product contains acetaminophen. Severe liver damage may occur if you take

- more than 6 capsules in 24 hours, which is the maximum daily amount
- with other drugs containing acetaminophen
- 3 or more alcoholic drinks every day while using this product

Allergy alert: Acetaminophen may cause severe skin reactions. Symptoms may include:

- skin reddening
- blisters
- rash

If a skin reaction occurs, stop use and seek medical help right away.

Do not use

- with any other drug containing acetaminophen (prescription or nonprescription). If you are not sure whether a drug contains acetaminophen, ask a doctor or pharmacist.
- if you are allergic to acetaminophen or any of the inactive ingredients in this product

Ask a doctor before use if you have

liver disease

Ask a doctor or pharmacist before use if you are

taking the blood thinning drug warfarin

Stop use and ask a doctor if

- pain gets worse or lasts more than 10 days
- fever gets worse or lasts more than 3 days
- new symptoms occur
- redness or swelling is present

These could be signs of a serious condition.

If pregnant or breast-feeding,

ask a health professional before use.

Overdose warning:

In the case of overdose, get medical help or contact a Poison Control Center right away (1-800-222-1222). Quick medical attention is critical for adults as well as for children even if you do not notice any signs or symptoms.

Directions

do not take more than directed (see overdose warning)

adults and children 12 years of age and over:

- take 2 capsules every 6 hours while symptoms last
- do not take more than 6 capsules in 24 hours, unless directed by a doctor
- do not take for more than 10 days unless directed by a doctor

children under 12 years: ask a doctor

Other information

store in a dry place at 15° – 30°C (59° – 86°F).

Inactive ingredients

FD&C blue #1, FD&C red #40, gelatin, polyvinylpyrrolidone, pregelatinized starch, sodium starch glycolate, stearic acid and titanium dioxide

Questions or comments?

Call 1-800-231-4670

Monday-Friday 9AM-5PM ET

Distributed by: MAJOR® PHARMACEUTICALS

Indianapolis, IN 46268
(800) 616-2471
www.major-rugby.com

TAMPER EVIDENT: DO NOT USE IF CAPSULE BAND OR PRINTED
SAFETY SEAL UNDER CAP IS BROKEN OR MISSING

PACKAGE LABEL

Major

NDC 0904-1987-60

extra strength

Mapap®

acetaminophen 500 mg each

pain reliever / fever reducer

aspirin free

100 capsules